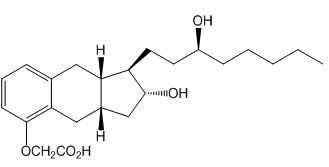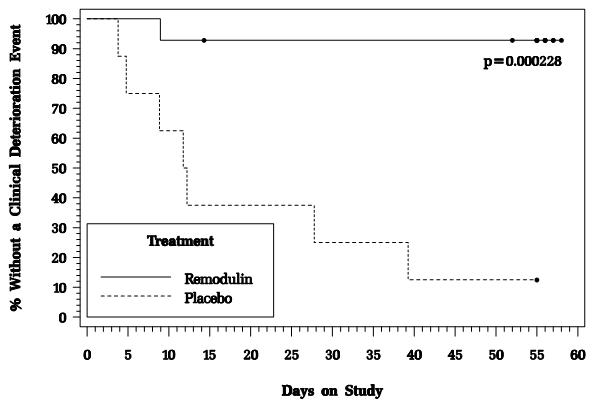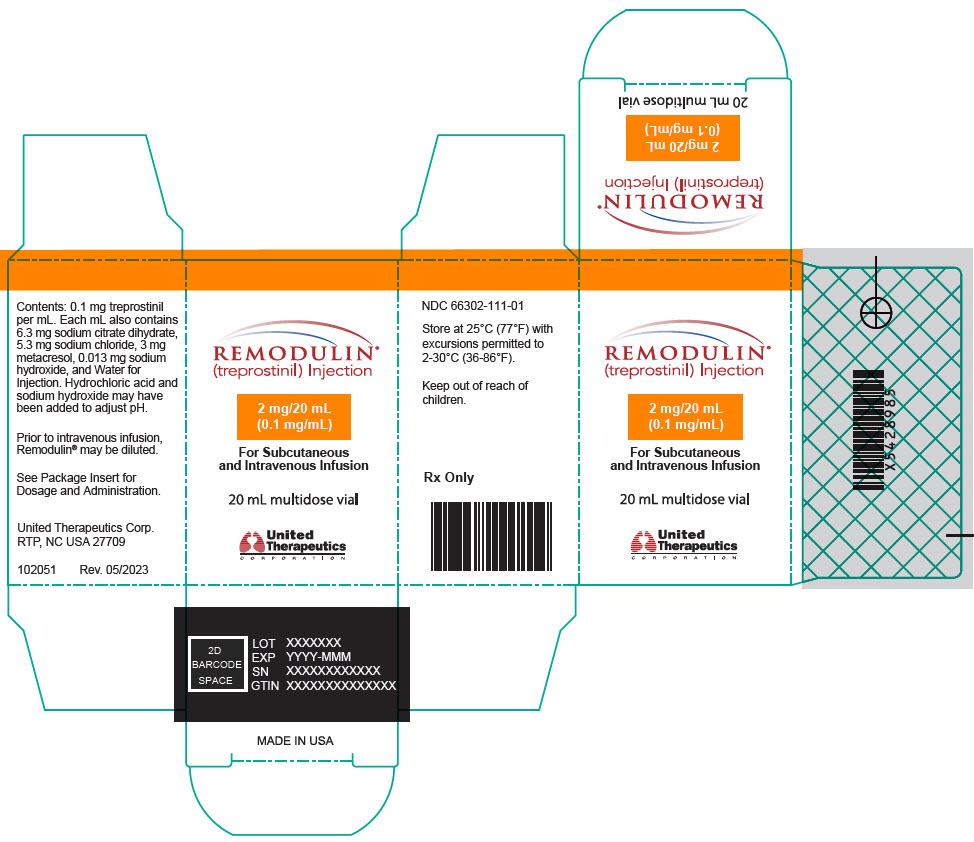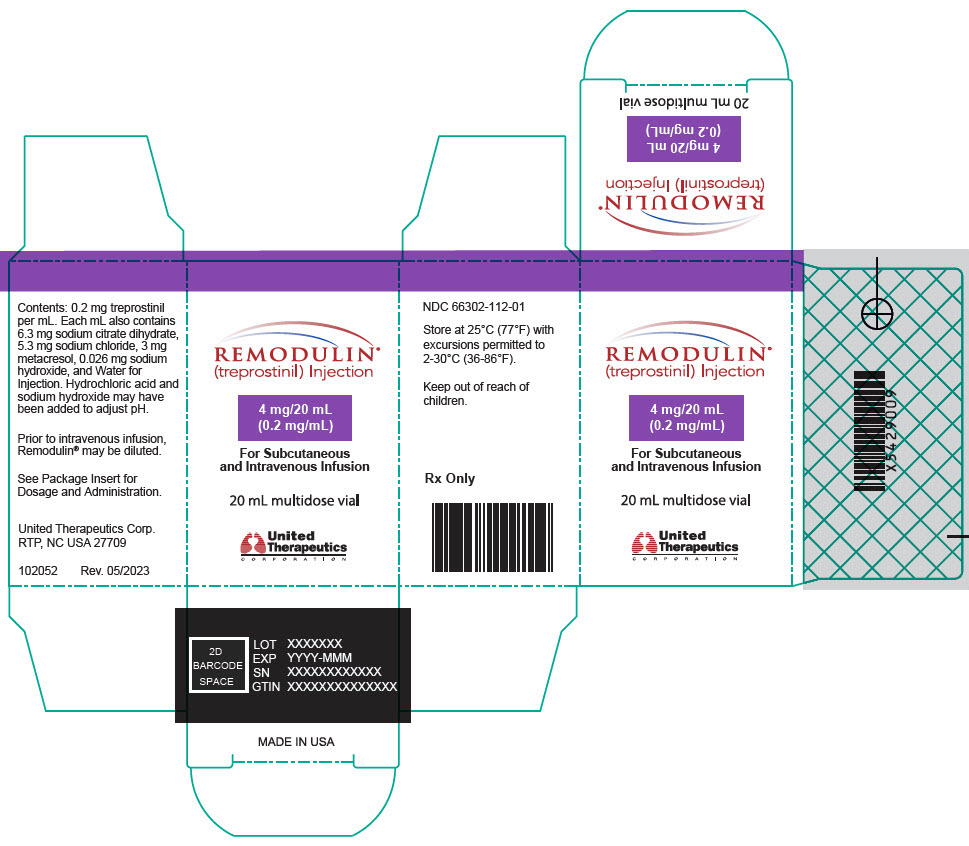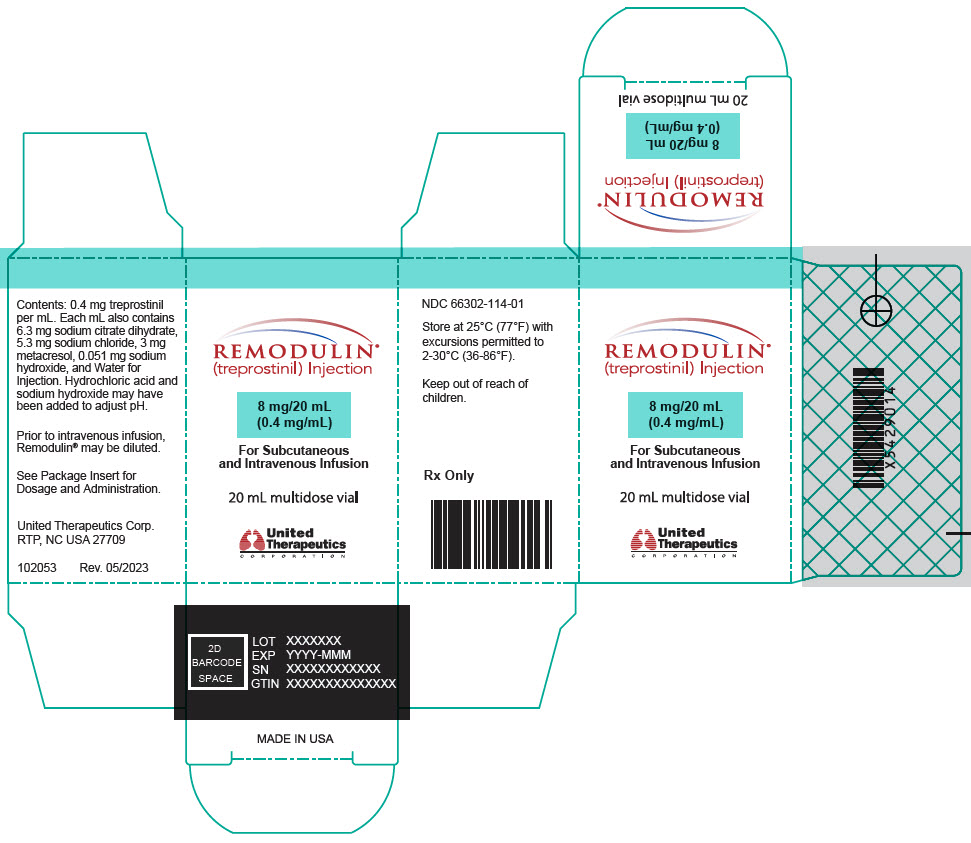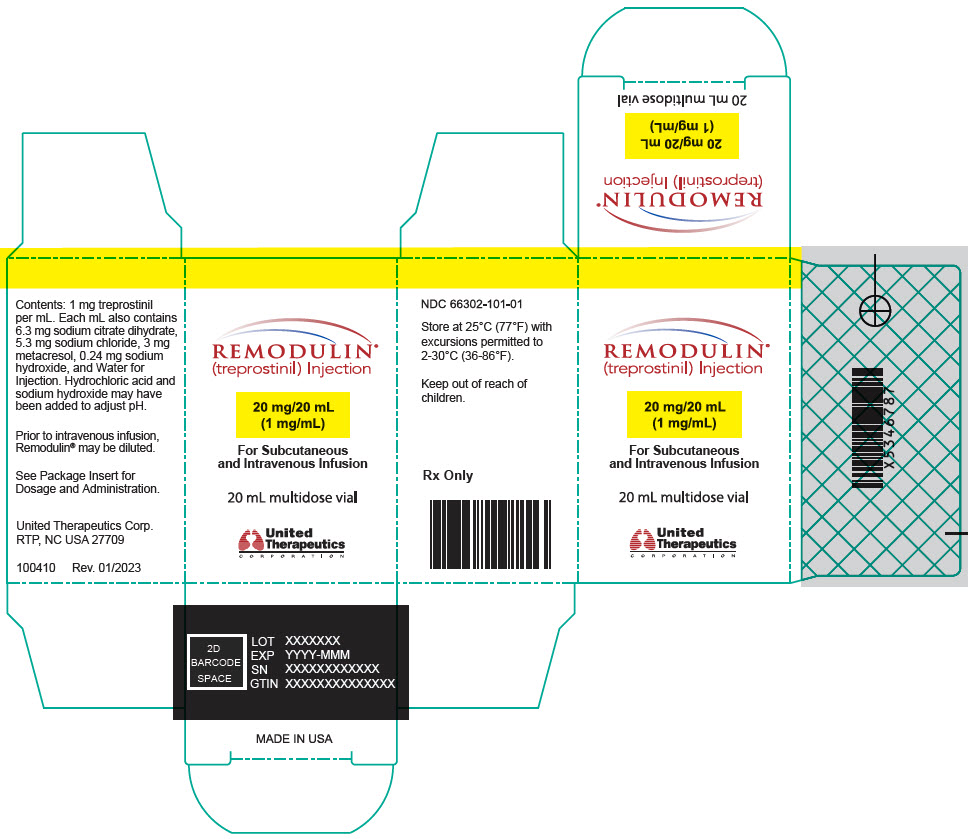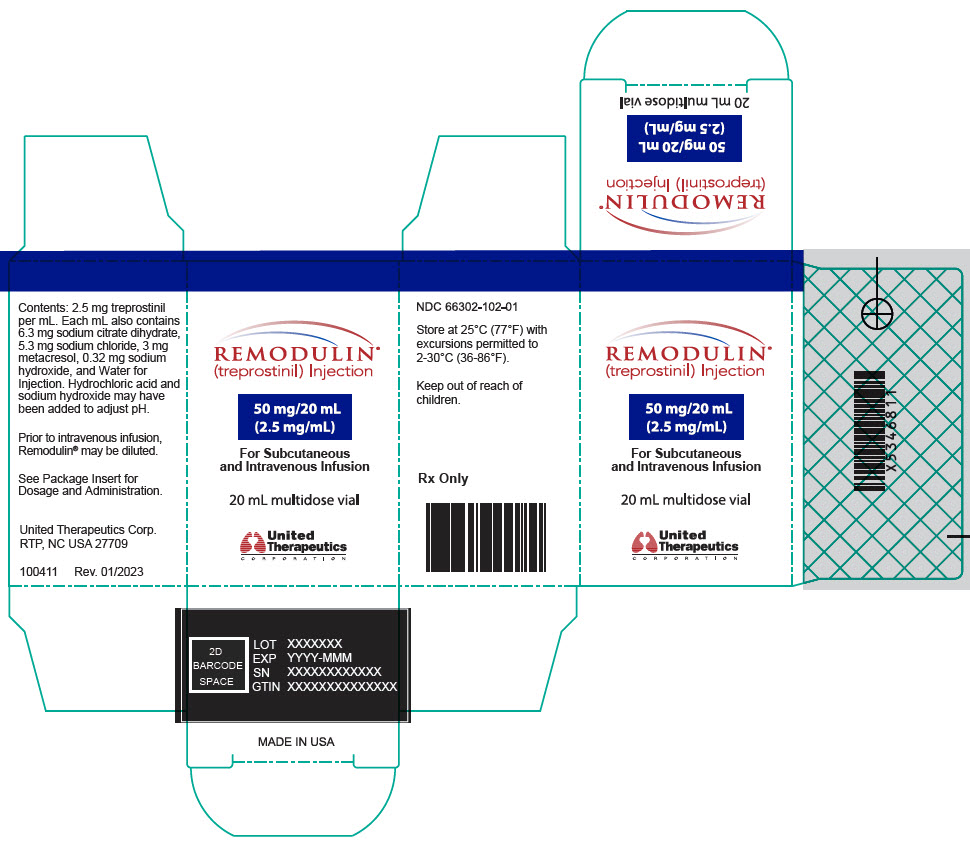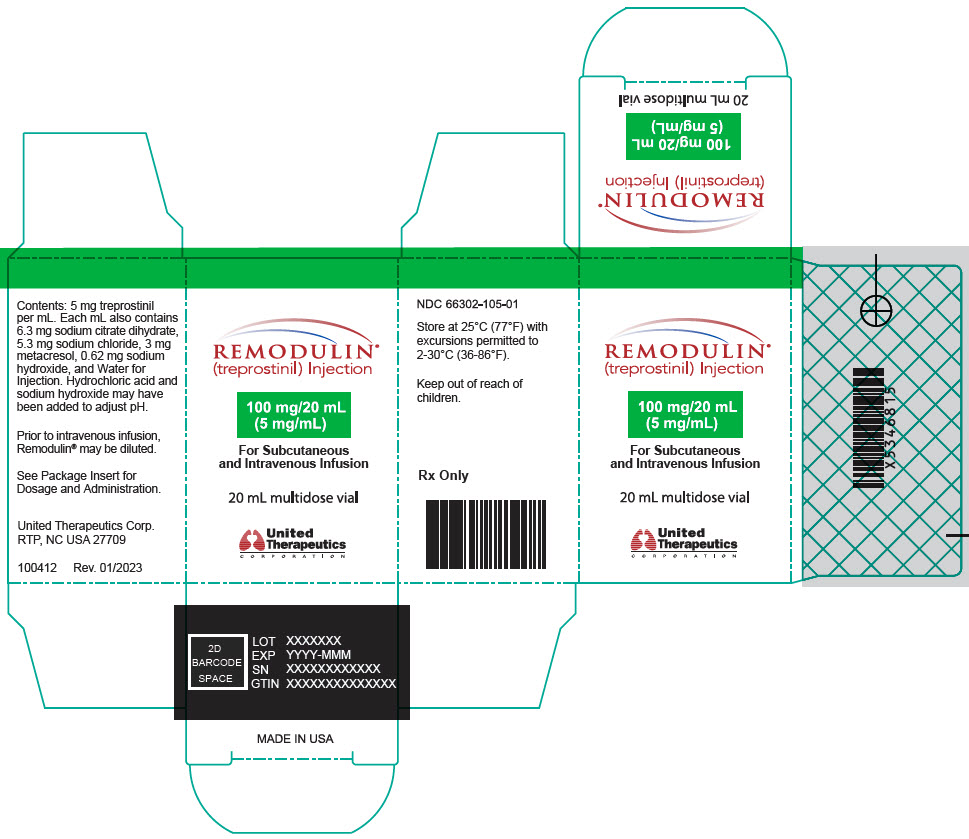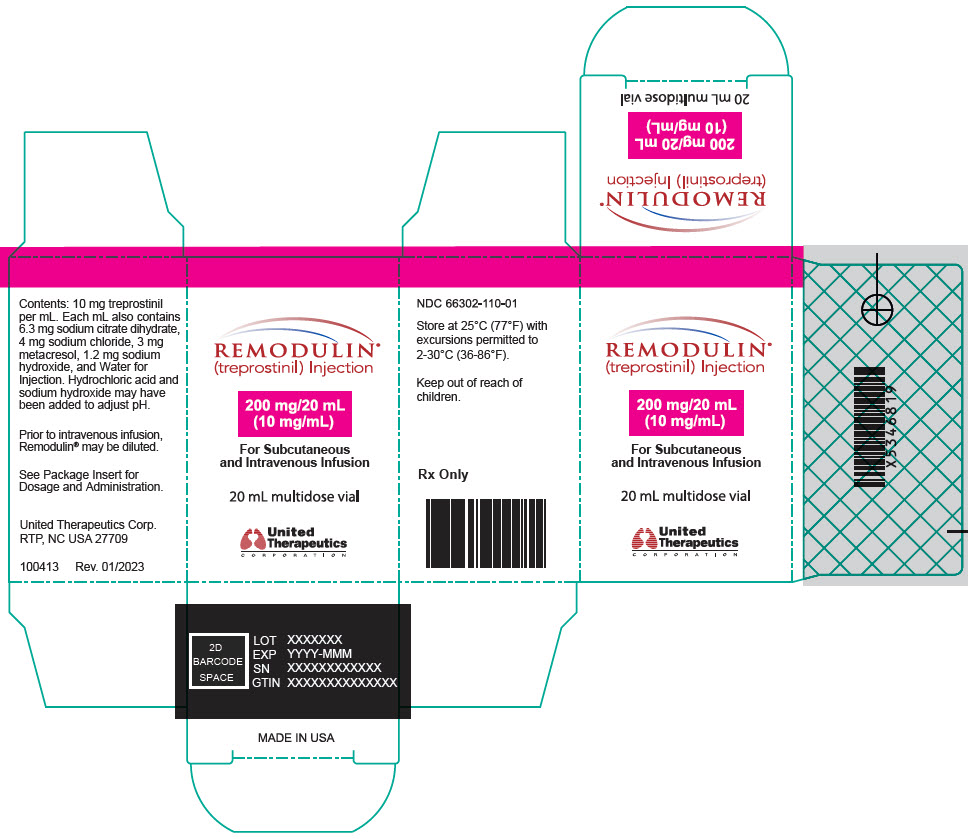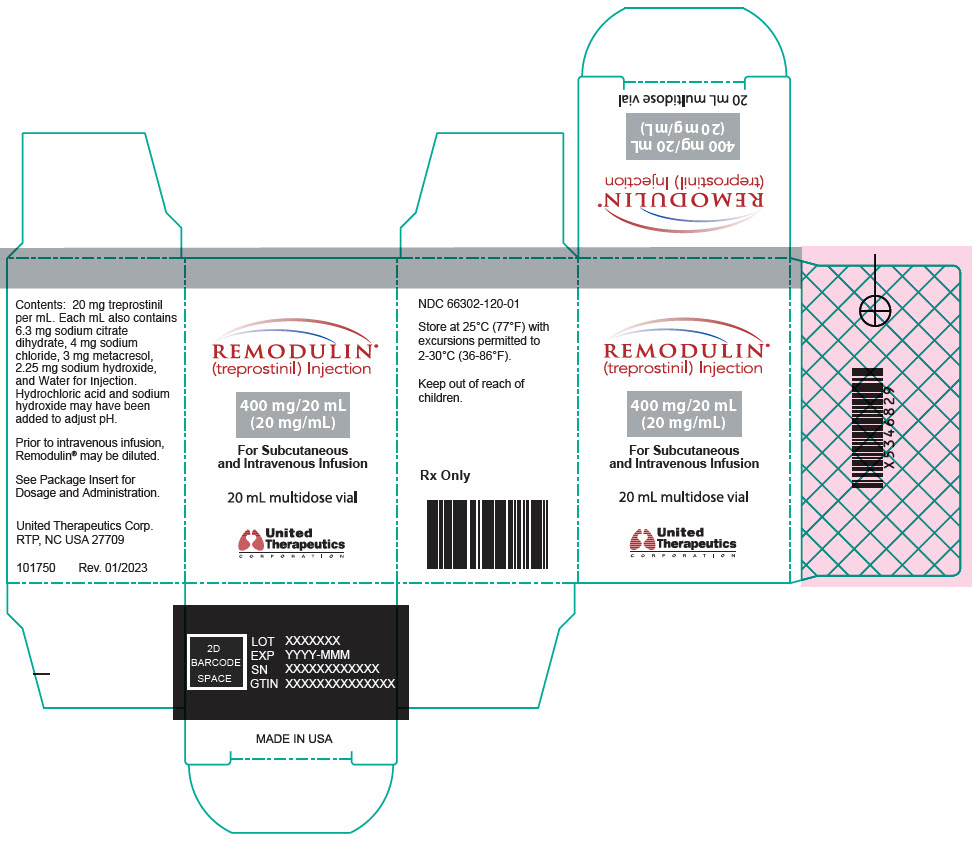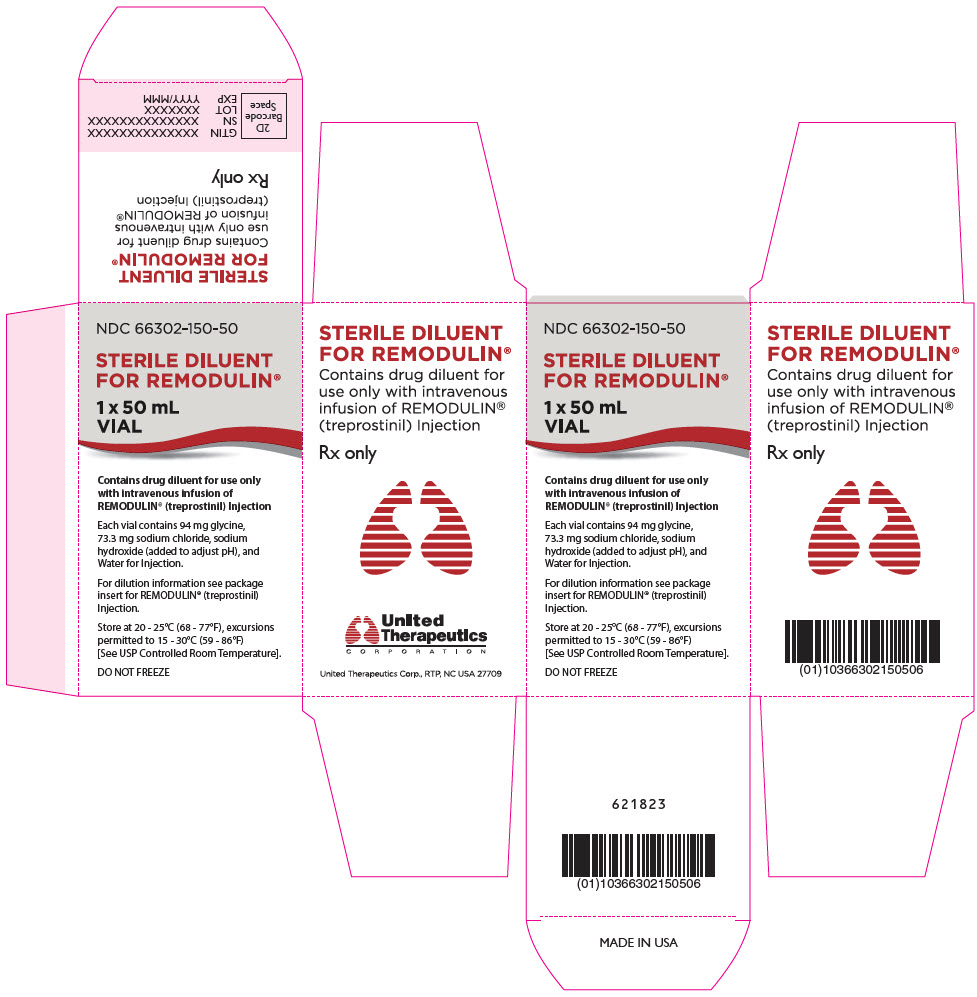 DRUG LABEL: Remodulin
NDC: 66302-111 | Form: INJECTION, SOLUTION
Manufacturer: United Therapeutics Corporation
Category: prescription | Type: HUMAN PRESCRIPTION DRUG LABEL
Date: 20250718

ACTIVE INGREDIENTS: treprostinil 2 mg/20 mL
INACTIVE INGREDIENTS: trisodium citrate dihydrate; sodium chloride; metacresol; sodium hydroxide; water; hydrochloric acid

HIGHLIGHTS OF PRESCRIBING INFORMATION

These highlights do not include all the information needed to use REMODULIN safely and effectively. See full prescribing information for REMODULIN.
REMODULIN® (treprostinil) Injection, for subcutaneous or intravenous use
Initial U.S. Approval: May 2002

1 INDICATIONS AND USAGE

Remodulin is a prostacyclin mimetic indicated for:

- Treatment of pulmonary arterial hypertension (PAH; WHO Group 1) to diminish symptoms associated with exercise. Studies establishing effectiveness included patients with NYHA Functional Class II-IV symptoms and etiologies of idiopathic or heritable PAH (58%), PAH associated with congenital systemic-to-pulmonary shunts (23%), or PAH associated with connective tissue diseases (19%). (1.1)
- Patients who require transition from epoprostenol, to reduce the rate of clinical deterioration. The risks and benefits of each drug should be carefully considered prior to transition. (1.2)

2 DOSAGE AND ADMINISTRATION

PAH WHO Group 1 in patients with NYHA Class II-IV symptoms:

- Initial dose for patients new to prostacyclin infusion therapy: 1.25 ng/kg/min; increase based on clinical response (increments of 1.25 ng/kg/min per week for the first 4 weeks of treatment, later 2.5 ng/kg/min per week). Avoid abrupt cessation. (2.2, 2.4)
- Mild to moderate hepatic insufficiency: Decrease initial dose to 0.625 ng/kg/min.
  Severe hepatic insufficiency: No studies performed. (2.5)

Transition from Epoprostenol:

Increase the Remodulin dose gradually as the epoprostenol dose is decreased, based on constant observation of response. (2.7)

Administration:

Continuous subcutaneous infusion is the preferred mode. Use intravenous (IV) infusion if subcutaneous infusion is not tolerated. (2.1, 2.6)

3 DOSAGE FORMS AND STRENGTHS

- Remodulin is supplied in 20-mL vials containing 2 mg (0.1 mg/mL), 4 mg (0.2 mg/mL), 8 mg (0.4 mg/mL), 20 mg (1 mg/mL), 50 mg (2.5 mg/mL), 100 mg (5 mg/mL), 200 mg (10 mg/mL), or 400 mg (20 mg/mL) of treprostinil. (3)

4 CONTRAINDICATIONS

None

5 WARNINGS AND PRECAUTIONS

- Chronic intravenous infusions delivered using an external infusion pump with an indwelling central venous catheter are associated with the risk of blood stream infections (BSIs) and sepsis, which may be fatal. (5.1)
- Do not abruptly lower the dose or withdraw dosing. (5.2)
- Remodulin may cause symptomatic hypotension. (5.4)
- Remodulin inhibits platelet aggregation and increases the risk of bleeding. (5.5)

6 ADVERSE REACTIONS

Most common adverse reactions (incidence >3%) reported in clinical studies with Remodulin: subcutaneous infusion site pain and reaction, headache, diarrhea, nausea, jaw pain, vasodilatation, edema, and hypotension. (6.1)

To report SUSPECTED ADVERSE REACTIONS, contact United Therapeutics Corp. at 1-866-458-6479 or contact FDA at 1-800-FDA-1088 or www.fda.gov/medwatch.

7 DRUG INTERACTIONS

- Remodulin dosage adjustment may be necessary if inhibitors or inducers of CYP2C8 are added or withdrawn. (7.1)

FULL PRESCRIBING INFORMATION

1 INDICATIONS AND USAGE

1.1 Pulmonary Arterial Hypertension

Remodulin is indicated for the treatment of pulmonary arterial hypertension (PAH; WHO Group 1) to diminish symptoms associated with exercise. Studies establishing effectiveness included patients with NYHA Functional Class II-IV symptoms and etiologies of idiopathic or heritable PAH (58%), PAH associated with congenital systemic-to-pulmonary shunts (23%), or PAH associated with connective tissue diseases (19%) [see Clinical Studies (14.1)].

1.2 Pulmonary Arterial Hypertension in Patients Requiring Transition from Epoprostenol

In patients with PAH requiring transition from epoprostenol, Remodulin is indicated to diminish the rate of clinical deterioration. Consider the risks and benefits of each drug prior to transition.

2 DOSAGE AND ADMINISTRATION

2.1 General

Remodulin can be administered with or without further dilution with Sterile Diluent for Remodulin or similar approved high-pH glycine diluent (e.g., Sterile Diluent for Flolan or Sterile Diluent for Epoprostenol), Sterile Water for Injection, or 0.9% Sodium Chloride Injection prior to administration. See Table 1 below for storage and administration time limits for the different diluents.

Diluted Remodulin has been shown to be stable at ambient temperature when stored for up to 14 days using high-pH glycine diluent at concentrations as low as 0.004 mg/mL (4,000 ng/mL).

Table 1: Selection of Diluent
Diluent | Storage Limits | Administration Limits
None | See Section 16 | 16 weeks at 40°C
Sterile Diluents for Remodulin, Flolan, or Epoprostenol | 14 days at room temperature | 48 hours at 40°C
Sterile Water for Injection 0.9% Sodium Chloride for Injection | 4 hours at room temperature or 24 hours refrigerated | 48 hours at 40°C

2.2 Initial Dose for Patients New to Prostacyclin Infusion Therapy

Remodulin is indicated for subcutaneous (SC) or intravenous (IV) use only as a continuous infusion. Remodulin is preferably infused subcutaneously, but can be administered by a central intravenous line if the subcutaneous route is not tolerated because of severe site pain or reaction. The infusion rate is initiated at 1.25 ng/kg/min. If this initial dose cannot be tolerated because of systemic effects, reduce the infusion rate to 0.625 ng/kg/min.

2.3 Initial Dose for Patients Transitioning to an Implantable Intravenous Infusion Pump

The initial dose of Remodulin should be the same as the current dose the patient is receiving using the external infusion pump at the time of transition.

2.4 Dosage Adjustments

The goal of chronic dosage adjustments is to establish a dose at which PAH symptoms are improved, while minimizing excessive pharmacologic effects of Remodulin (headache, nausea, emesis, restlessness, anxiety, and infusion site pain or reaction).

The infusion rate should be increased in increments of 1.25 ng/kg/min per week for the first four weeks of treatment and then 2.5 ng/kg/min per week for the remaining duration of infusion, depending on clinical response. Dosage adjustments may be undertaken more often if tolerated. Avoid abrupt cessation of infusion [see Warnings and Precautions (5.2)]. Restarting a Remodulin infusion within a few hours after an interruption can be done using the same dose rate. Interruptions for longer periods may require the dose of Remodulin to be re-titrated.

2.5 Patients with Hepatic Insufficiency

In patients with mild or moderate hepatic insufficiency, decrease the initial dose of Remodulin to 0.625 ng/kg/min ideal body weight. Remodulin has not been studied in patients with severe hepatic insufficiency [see Warnings and Precautions (5.3), Use in Specific Populations (8.6), and Clinical Pharmacology (12.3)].

2.6 Administration

Inspect parenteral drug products for particulate matter and discoloration prior to administration whenever solution and container permit. If either particulate matter or discoloration is noted, do not use.

Preparation

Remodulin is administered by subcutaneous or intravenous infusion at a calculated rate based on a patient's dose (ng/kg/min), weight (kg), and the Remodulin concentration (mg/mL).

For administration of Undiluted Remodulin the rate is calculated using the following formula:

 | Undiluted Infusion Rate (mL/hour) | = | Dose (ng/kg/min) | × | Weight (kg) | × | 0.00006 [Conversion factor of 0.00006 = 60 min/hour × 0.000001 mg/ng]
 | Undiluted Infusion Rate (mL/hour) | = | Remodulin Vial Strength (mg/mL)

For administration of Diluted Remodulin, the concentration is calculated using the following formula:

Step 1

 | Diluted Remodulin Concentration (mg/mL) |  | Dose (ng/kg/min) | × | Weight (kg) | × | 0.00006
 | Diluted Remodulin Concentration (mg/mL) | = | Dose (ng/kg/min) | × | Weight (kg) | × | 0.00006
 | Diluted Remodulin Concentration (mg/mL) | = | Infusion Rate (mL/hour)

The volume of Remodulin Injection needed to make the required diluted Remodulin concentration for the given reservoir size can then be calculated using the following formula:

Step 2

Volume of Remodulin Injection (mL) | = | Diluted Remodulin Concentration (mg/mL) | × | Total Volume of Diluted Remodulin Solution in Reservoir (mL)
Volume of Remodulin Injection (mL) | = | Remodulin Vial Strength (mg/mL) | × | Total Volume of Diluted Remodulin Solution in Reservoir (mL)

The calculated volume of Remodulin Injection is then added to the reservoir along with the sufficient volume of diluent to achieve the desired total volume in the reservoir.

Subcutaneous Infusion

Remodulin is administered subcutaneously by continuous infusion, via a subcutaneous catheter, using an infusion pump designed for subcutaneous drug delivery. The infusion pump should: (1) be adjustable to approximately 0.002 mL/hour, (2) have occlusion/no delivery, low battery, programming error and motor malfunction alarms, (3) have delivery accuracy of ±6% or better, (4) be positive pressure-driven, and (5) have a reservoir made of polyvinyl chloride, polypropylene or glass. Alternatively, use an infusion pump cleared for use with Remodulin. To avoid potential interruptions in drug delivery, the patient must have immediate access to a backup infusion pump and subcutaneous infusion sets.

Intravenous Infusion

External Intravenous Infusion Pump:

Remodulin is administered intravenously by continuous infusion via a surgically placed indwelling central venous catheter using an external infusion pump designed for intravenous drug delivery. If clinically necessary, a temporary peripheral intravenous cannula, preferably placed in a large vein, may be used for short term administration of Remodulin. Use of a peripheral intravenous infusion for more than a few hours increases the risk of thrombophlebitis. The infusion pump used to administer Remodulin should: (1) have occlusion/no delivery, low battery, programming error and motor malfunction alarms, (2) have delivery accuracy of ±6% or better, (3) be positive pressure driven, and (4) have a reservoir made of polyvinyl chloride, polypropylene or glass. Alternatively, use an infusion pump cleared for use with Remodulin. To avoid potential interruptions in drug delivery, the patient must have immediate access to a backup infusion pump and infusion sets.

Infusion sets with an in-line 0.22- or 0.2-micron pore size filter should be used.

Implantable Intravenous Infusion Pump:

Use an implantable intravenous infusion pump approved for use with Remodulin, such as the Implantable System for Remodulin® (ISR). Refer to the pump manufacturer's manual for specific instructions regarding preparation, programing, implantation, and refilling.

2.7 Patients Requiring Transition from Epoprostenol

Transition from epoprostenol to Remodulin is accomplished by initiating the infusion of Remodulin and increasing it, while simultaneously reducing the dose of intravenous epoprostenol. The transition to Remodulin should take place in a hospital with constant observation of response (e.g., walk distance and signs and symptoms of disease progression). Initiate Remodulin at a recommended dose of 10% of the current epoprostenol dose, and then escalate as the epoprostenol dose is decreased (see Table 2 for recommended dose titrations).

Patients are individually titrated to a dose that allows transition from epoprostenol therapy to Remodulin while balancing prostacyclin-limiting adverse events. Treat increases in the patient's symptoms of PAH first with increases in the dose of Remodulin. Treat side effects normally associated with prostacyclin and prostacyclin analogs first by decreasing the dose of epoprostenol.

Table 2: Recommended Transition Dose Changes
Step | Epoprostenol Dose | Remodulin Dose
1 | Unchanged | 10% Starting Epoprostenol Dose
2 | 80% Starting Epoprostenol Dose | 30% Starting Epoprostenol Dose
3 | 60% Starting Epoprostenol Dose | 50% Starting Epoprostenol Dose
4 | 40% Starting Epoprostenol Dose | 70% Starting Epoprostenol Dose
5 | 20% Starting Epoprostenol Dose | 90% Starting Epoprostenol Dose
6 | 5% Starting Epoprostenol Dose | 110% Starting Epoprostenol Dose
7 | 0 | 110% Starting Epoprostenol Dose + additional 5-10% increments as needed

3 DOSAGE FORMS AND STRENGTHS

20-mL vial containing 2 mg treprostinil (0.1 mg per mL).

20-mL vial containing 4 mg treprostinil (0.2 mg per mL).

20-mL vial containing 8 mg treprostinil (0.4 mg per mL).

20-mL vial containing 20 mg treprostinil (1 mg per mL).

20-mL vial containing 50 mg treprostinil (2.5 mg per mL).

20-mL vial containing 100 mg treprostinil (5 mg per mL).

20-mL vial containing 200 mg treprostinil (10 mg per mL).

20-mL vial containing 400 mg treprostinil (20 mg per mL).

4 CONTRAINDICATIONS

None

5 WARNINGS AND PRECAUTIONS

5.1 Risk of Catheter-Related Bloodstream Infection

Chronic intravenous infusions of Remodulin delivered using an external infusion pump with an indwelling central venous catheter are associated with the risk of blood stream infections (BSIs) and sepsis, which may be fatal. Therefore, continuous subcutaneous infusion is the preferred mode of administration.

In an open-label study of IV treprostinil (n=47) using an external infusion pump, there were seven catheter-related line infections during approximately 35 patient years, or about 1 BSI event per 5 years of use. A CDC survey of seven sites that used IV treprostinil for the treatment of PAH found approximately 1 BSI (defined as any positive blood culture) event per 3 years of use. Administration of IV Remodulin with a high pH glycine diluent has been associated with a lower incidence of BSIs when compared to neutral diluents (sterile water, 0.9% sodium chloride) when used along with catheter care guidelines.

In an open-label study of an implantable pump (n=60), there were two blood stream infections (BSIs) related to the implant procedure during approximately 265 patient years.

5.2 Worsening PAH upon Abrupt Withdrawal or Sudden Large Dose Reduction

Avoid abrupt withdrawal or sudden large reductions in dosage of Remodulin, which may result in worsening of PAH symptoms.

5.3 Patients with Hepatic Insufficiency

Titrate Remodulin slowly in patients with hepatic insufficiency, because such patients will likely be exposed to greater systemic concentrations relative to patients with normal hepatic function [see Dosage and Administration (2.5), Use in Specific Populations (8.6), and Clinical Pharmacology (12.3)].

5.4 Risk of Symptomatic Hypotension

Treprostinil is a pulmonary and systemic vasodilator. In patients with low systemic arterial pressure, treatment with Remodulin may produce symptomatic hypotension.

5.5 Risk of Bleeding

Remodulin inhibits platelet aggregation and increases the risk of bleeding.

6 ADVERSE REACTIONS

The following adverse reactions are discussed elsewhere in labeling: Infections associated with intravenous administration [see Warnings and Precautions (5.1)].

6.1 Clinical Trials Experience

Because clinical trials are conducted under widely varying conditions, adverse reaction rates observed in the clinical trials of a drug cannot be directly compared to rates in the clinical trials of another drug and may not reflect the rates observed in practice.

Adverse Events with Subcutaneously Administered Remodulin

Patients receiving Remodulin as a subcutaneous infusion reported a wide range of adverse events, many potentially related to the underlying disease (dyspnea, fatigue, chest pain, right ventricular heart failure, and pallor). During clinical trials with subcutaneous infusion of Remodulin, infusion site pain and reaction were the most common adverse events among those treated with Remodulin. Infusion site reaction was defined as any local adverse event other than pain or bleeding/bruising at the infusion site and included symptoms such as erythema, induration, or rash. Infusion site reactions were sometimes severe and could lead to discontinuation of treatment.

Table 3: Percentages of Subjects Reporting Subcutaneous Infusion Site Adverse Events
 | Reaction |  | Pain
 | Placebo | Remodulin | Placebo | Remodulin
Severe | 1 | 38 | 2 | 39
Requiring narcotics [based on prescriptions for narcotics, not actual use] | NA [medications used to treat infusion site pain were not distinguished from those used to treat site reactions] | NA | 1 | 32
Leading to discontinuation | 0 | 3 | 0 | 7

Other adverse events included diarrhea, jaw pain, edema, vasodilatation, and nausea, and these are generally considered to be related to the pharmacologic effects of Remodulin, whether administered subcutaneously or intravenously.

Adverse Reactions during Chronic Dosing

Table 4 lists adverse reactions that occurred at a rate of at least 3% more frequent in patients treated with subcutaneous Remodulin than with placebo in controlled trials in PAH.

Table 4: Adverse Reactions in Controlled 12-Week Studies of Subcutaneous Remodulin and at least 3% more frequent than on Placebo
Adverse Reaction | Remodulin (N=236) Percent of Patients | Placebo (N=233) Percent of Patients
Infusion Site Pain | 85 | 27
Infusion Site Reaction | 83 | 27
Headache | 27 | 23
Diarrhea | 25 | 16
Nausea | 22 | 18
Rash | 14 | 11
Jaw Pain | 13 | 5
Vasodilatation | 11 | 5
Edema | 9 | 3

Reported adverse reactions (at least 3% more frequent on drug than on placebo) are included with the exception of those too general to be informative, and those not plausibly attributable to the use of the drug, because they were associated with the condition being treated or are very common in the treated population.

While hypotension occurred in both groups, the event was experienced twice as frequently in the Remodulin group as compared to the placebo group (4% in Remodulin treatment group versus 2% in placebo-controlled group). As a potent vasodilator, hypotension is possible with the administration of Remodulin.

The safety of Remodulin was also studied in a long-term, open-label extension study in which 860 patients were dosed for a mean duration of 1.6 years, with a maximum exposure of 4.6 years. Twenty-nine (29%) percent achieved a dose of at least 40 ng/kg/min (max: 290 ng/kg/min). The safety profile during this chronic dosing study was similar to that observed in the 12-week placebo-controlled study except for the following suspected adverse drug reactions (occurring in at least 3% of patients): anorexia, vomiting, infusion site infection, asthenia, and abdominal pain.

Adverse Events Attributable to the Drug Delivery System

In controlled studies of Remodulin administered subcutaneously, there were no reports of infection related to the drug delivery system. There were 187 infusion system complications reported in 28% of patients (23% Remodulin, 33% placebo); 173 (93%) were pump related and 14 (7%) related to the infusion set. Eight of these patients (4 Remodulin, 4 placebo) reported non-serious adverse events resulting from infusion system complications. Adverse events resulting from problems with the delivery systems were typically related to either symptoms of excess Remodulin (e.g., nausea) or return of PAH symptoms (e.g., dyspnea). These events were generally resolved by correcting the delivery system pump or infusion set problem, such as replacing the syringe or battery, reprogramming the pump, or straightening a crimped infusion line. Adverse events resulting from problems with the delivery system did not lead to clinical instability or rapid deterioration. In addition to these adverse events due to the drug delivery system during subcutaneous administration, the following adverse events may be attributable to the IV mode of infusion including arm swelling, paresthesia, hematoma, and pain [see Warnings and Precautions (5.1)].

6.2 Post-Marketing Experience

In addition to adverse reactions reported from clinical trials, the following events have been identified during post-approval use of Remodulin. Because they are reported voluntarily from a population of unknown size, estimates of frequency cannot be made. The following events have been chosen for inclusion because of a combination of their seriousness, frequency of reporting, and potential connection to Remodulin. These events are thrombophlebitis associated with peripheral intravenous infusion, thrombocytopenia, bone pain, pruritus, dizziness, arthralgia, myalgia/muscle spasm, and pain in extremity. In addition, generalized rashes, sometimes macular or papular in nature, and cellulitis have been infrequently reported.

7 DRUG INTERACTIONS

7.1 Effect of CYP2C8 Inhibitors and Inducers on Treprostinil

Dose adjustment of treprostinil may be necessary when co-administered with CYP2C8 inducers or inhibitors. Human pharmacokinetic studies with an oral formulation of treprostinil (treprostinil diolamine) indicated that co-administration of the cytochrome P450 (CYP) 2C8 enzyme inhibitor gemfibrozil increases exposure (both Cmax and AUC) to treprostinil. Co-administration of the CYP2C8 enzyme inducer rifampin decreases exposure to treprostinil. It has not been determined if the changes in exposure of treprostinil with inhibitors or inducers of CYP2C8 observed for the oral administration of treprostinil would be similar for treprostinil administered via the parenteral route [see Clinical Pharmacology (12.3)].

8 USE IN SPECIFIC POPULATIONS

8.1 Pregnancy

Risk Summary

Limited case reports of treprostinil use in pregnant women are insufficient to inform a drug-associated risk of adverse developmental outcomes. However, there are risks to the mother and the fetus associated with pulmonary arterial hypertension (see Clinical Considerations). In animal studies, no adverse reproductive and developmental effects were seen in rats at about 123 and 48 times the human exposure based on Cmax and AUC, respectively. In rabbits, external fetal and soft tissue malformations and skeletal malformations were observed at about 7 and 5 times the human exposure based on Cmax and AUC, respectively (see Data).

The estimated background risk of major birth defects and miscarriage for the indicated populations is unknown. All pregnancies have a background risk of birth defect, loss, or other adverse outcomes. In the U.S. general population, the estimated background risk of major birth defects and miscarriage in clinically recognized pregnancies is 2 to 4% and 15 to 20%, respectively.

Clinical Considerations

Disease-associated maternal and embryo-fetal risk

Pulmonary arterial hypertension is associated with an increased risk of maternal and fetal mortality.

Data

Animal reproduction studies have been conducted with treprostinil via continuous subcutaneous administration and with treprostinil diolamine administered orally. In pregnant rats, continuous subcutaneous infusions of treprostinil during organogenesis and late gestational development, at doses as high as 900 ng treprostinil/kg/min (about 117 times the starting human subcutaneous infusion rate, on a ng/m^2 basis and about 16 times the average rate achieved in clinical trials), resulted in no evidence of harm to the fetus. In pregnant rabbits, effects of continuous subcutaneous infusions of treprostinil during organogenesis were limited to an increased incidence of fetal skeletal variations (bilateral full rib or right rudimentary rib on lumbar 1) associated with maternal toxicity (reduction in body weight and food consumption) at a dose of 150 ng treprostinil/kg/min (about 41 times the starting human subcutaneous infusion rate, on a ng/m^2 basis, and 5 times the average rate used in clinical trials). In rats, continuous subcutaneous infusion of treprostinil from implantation to the end of lactation, at doses of up to 450 ng treprostinil/kg/min, did not affect the growth and development of offspring. In studies with orally administered treprostinil diolamine, no adverse effect doses for fetal viability/growth, fetal development (teratogenicity), and postnatal development were determined in rats. In pregnant rats, no evidence of harm to the fetus was observed following oral administration of treprostinil diolamine at the highest dose tested (20 mg/kg/day), which represents about 123 and 48 times the human exposure, when based on Cmax and AUC of the average subcutaneous infusion rate achieved in clinical trials, respectively. In pregnant rabbits, external fetal and soft tissue malformations and fetal skeletal malformation occurred. The dose at which no adverse effects were seen (0.5 mg/kg/day) represents about 7 and 5 times the human exposure, when based on Cmax and AUC of the average subcutaneous infusion rate achieved in clinical trials, respectively. No treprostinil treatment-related effects on labor and delivery were seen in animal studies. Animal reproduction studies are not always predictive of human response.

8.2 Lactation

Risk Summary

There are no data on the presence of treprostinil in human milk, the effects on the breastfed infant, or the effects on milk production.

8.4 Pediatric Use

Safety and effectiveness in pediatric patients have not been established. Clinical studies of Remodulin did not include sufficient numbers of patients aged ≤16 years to determine whether they respond differently from older patients.

8.5 Geriatric Use

Clinical studies of Remodulin did not include sufficient numbers of patients aged 65 and over to determine whether they respond differently from younger patients. In general, dose selection for an elderly patient should be cautious, reflecting the greater frequency of decreased hepatic, renal, or cardiac function, and of concomitant disease or other drug therapy.

8.6 Patients with Hepatic Insufficiency

Remodulin clearance is reduced in patients with hepatic insufficiency. In patients with mild or moderate hepatic insufficiency, decrease the initial dose of Remodulin to 0.625 ng/kg/min ideal body weight, and monitor closely. Remodulin has not been studied in patients with severe hepatic insufficiency [see Dosage and Administration (2.5), Warnings and Precautions (5.3), and Clinical Pharmacology (12.3)].

8.7 Patients with Renal Impairment

No dose adjustments are required in patients with renal impairment. Treprostinil is not cleared by dialysis [see Clinical Pharmacology (12.3)].

10 OVERDOSAGE

Signs and symptoms of overdose with Remodulin during clinical trials are extensions of its dose-limiting pharmacologic effects and include flushing, headache, hypotension, nausea, vomiting, and diarrhea. Most events were self-limiting and resolved with reduction or withholding of Remodulin.

In controlled clinical trials using an external infusion pump, seven patients received some level of overdose and in open-label follow-on treatment seven additional patients received an overdose; these occurrences resulted from accidental bolus administration of Remodulin, errors in pump programmed rate of administration, and prescription of an incorrect dose. In only two cases did excess delivery of Remodulin produce an event of substantial hemodynamic concern (hypotension, near-syncope).

One pediatric patient was accidentally administered 7.5 mg of Remodulin via a central venous catheter. Symptoms included flushing, headache, nausea, vomiting, hypotension, and seizure-like activity with loss of consciousness lasting several minutes. The patient subsequently recovered.

11 DESCRIPTION

Remodulin (treprostinil) Injection is a sterile solution of treprostinil, a prostacyclin mimetic, formulated for subcutaneous or intravenous administration. Remodulin is supplied in 20-mL multidose vials in eight strengths, containing 2 mg (0.1 mg/mL), 4 mg (0.2 mg/mL), 8 mg (0.4 mg/mL), 20 mg (1 mg/mL), 50 mg (2.5 mg/mL), 100 mg (5 mg/mL), 200 mg (10 mg/mL), or 400 mg (20 mg/mL) of treprostinil. Each mL also contains 5.3 mg sodium chloride (except for the 10 mg/mL and 20 mg/mL strengths, which contain 4.0 mg sodium chloride), 3 mg metacresol, 6.3 mg sodium citrate dihydrate, and water for injection. Sodium hydroxide and hydrochloric acid may be added to adjust pH between 6.0 and 7.2.

Treprostinil is chemically stable at room temperature and neutral pH.

Treprostinil is (1R,2R,3aS,9aS)-[[2,3,3a,4,9,9a-hexahydro-2-hydroxy-1-[(3S)-3-hydroxyoctyl]-1H-benz[f]inden-5-yl]oxy]acetic acid. Treprostinil has a molecular weight of 390.52 and a molecular formula of C23H34O5.

The structural formula of treprostinil is:

Sterile Diluent for Remodulin is a high-pH (pH~10.4) glycine diluent supplied in a 50-mL vial containing 50 mL of Sterile Diluent for Remodulin. Each vial contains 94 mg glycine, 73.3 mg sodium chloride, sodium hydroxide (to adjust pH), and water for injection.

12 CLINICAL PHARMACOLOGY

12.1 Mechanism of Action

The major pharmacologic actions of treprostinil are direct vasodilation of pulmonary and systemic arterial vascular beds, and inhibition of platelet aggregation.

12.2 Pharmacodynamics

In animals, the vasodilatory effects reduce right and left ventricular afterload and increase cardiac output and stroke volume. Other studies have shown that treprostinil causes a dose-related negative inotropic and lusitropic effect. No major effects on cardiac conduction have been observed.

Treprostinil produces vasodilation and tachycardia. Single doses of treprostinil up to 84 mcg by inhalation produce modest and short-lasting effects on QTc, but this is apt to be an artifact of the rapidly changing heart rate. Treprostinil administered by the subcutaneous or intravenous routes has the potential to generate concentrations many-fold greater than those generated via the inhaled route; the effect on the QTc interval when treprostinil is administered parenterally has not been established.

12.3 Pharmacokinetics

The pharmacokinetics of continuous subcutaneous Remodulin are linear over the dose range of 2.5 to 125 ng/kg/min (corresponding to plasma concentrations of about 260 pg/mL to 18,250 pg/mL) and can be described by a two-compartment model. Dose proportionality at infusion rates greater than 125 ng/kg/min has not been studied.

Subcutaneous and intravenous administration of Remodulin demonstrated bioequivalence at steady state at a dose of 10 ng/kg/min.

Absorption

Remodulin is relatively rapidly and completely absorbed after subcutaneous infusion, with an absolute bioavailability approximating 100%. Steady-state concentrations occurred in approximately 10 hours. Concentrations in patients treated with an average dose of 9.3 ng/kg/min were approximately 2,000 ng/L.

Distribution

The volume of distribution of the drug in the central compartment is approximately 14 L/70 kg ideal body weight. Remodulin at in vitro concentrations well above what is clinically relevant was 91% bound to human plasma protein.

Metabolism and Excretion

Treprostinil is substantially metabolized by the liver, primarily by CYP2C8. In a study conducted in healthy volunteers using [^14C] treprostinil, 79% and 13% of the subcutaneous dose was recovered in the urine and feces, respectively, over 10 days. Only 4% was excreted as unchanged treprostinil in the urine. Five metabolites were detected in the urine, ranging from 10% to 16% and representing 64% of the dose administered. Four of the metabolites are products of oxidation of the 3-hydroxyloctyl side chain and one is a glucuroconjugated derivative (treprostinil glucuronide). The identified metabolites do not appear to have activity.

The elimination of treprostinil (following subcutaneous administration) is biphasic, with a terminal elimination half-life of approximately 4 hours using a two-compartment model. Systemic clearance is approximately 30 L/hour for a 70 kg person.

Based on in vitro studies treprostinil does not inhibit or induce major CYP enzymes.

Specific Populations

Hepatic Insufficiency

In patients with portopulmonary hypertension and mild (n=4) or moderate (n=5) hepatic insufficiency, Remodulin at a subcutaneous dose of 10 ng/kg/min for 150 minutes had a Cmax that was 2-fold and 4-fold, respectively, and an AUC 0-∞ that was 3-fold and 5-fold, respectively, values observed in healthy subjects. Clearance in patients with hepatic insufficiency was reduced by up to 80% compared to healthy adults.

Renal Impairment

In patients with severe renal impairment requiring dialysis (n=8), administration of a single 1 mg dose of orally administered treprostinil pre- and post-dialysis resulted in an AUC0-inf that was not significantly altered compared to healthy subjects.

Drug Interaction Studies

Effect of CYP2C8 Inhibitors and Inducers on Treprostinil

Co-administration of an oral formulation of treprostinil (treprostinil diolamine) with gemfibrozil (600 mg twice a day), a CYP2C8 enzyme inhibitor, doubles the AUC and Cmax of treprostinil in healthy adults. Co-administration of an oral formulation of treprostinil (treprostinil diolamine) with rifampin (600 mg/day), a CYP2C8 enzyme inducer, decreases AUC of treprostinil by 22%.

Effect of Treprostinil on Cytochrome P450 Enzymes

In vitro studies of human hepatic microsomes showed that treprostinil does not inhibit cytochrome P450 (CYP) isoenzymes CYP1A2, CYP2A6, CYP2C8, CYP2C9, CYP2C19, CYP2D6, CYP2E1, and CYP3A. Additionally, treprostinil does not induce CYP1A2, CYP2B6, CYP2C9, CYP2C19, and CYP3A isoenzymes.

Effect of Other Drugs on Treprostinil

Human pharmacokinetic studies with an oral formulation of treprostinil (treprostinil diolamine) indicated that co-administration of the cytochrome P450 (CYP) 2C8 enzyme inhibitor gemfibrozil increases exposure (both Cmax and AUC) to treprostinil. Co-administration of the CYP2C8 enzyme inducer rifampin decreases exposure to treprostinil.

Drug interaction studies have been carried out with treprostinil (oral or subcutaneous) co-administered with acetaminophen (4 g/day), esomeprazole (40 mg/day), bosentan (250 mg/day), sildenafil (60 mg/day), warfarin (25 mg/day), and fluconazole (200 mg/day), respectively, in healthy volunteers. These studies did not show a clinically significant effect on the pharmacokinetics of treprostinil. Treprostinil does not affect the pharmacokinetics or pharmacodynamics of warfarin. The pharmacokinetics of R- and S- warfarin and the INR in healthy subjects given a single 25 mg dose of warfarin were unaffected by continuous subcutaneous infusion of treprostinil at an infusion rate of 10 ng/kg/min.

13 NONCLINICAL TOXICOLOGY

13.1 Carcinogenesis, Mutagenesis, Impairment of Fertility

A two-year rat carcinogenicity study was performed with treprostinil inhalation at target doses of 5.26, 10.6, and 34.1 mcg/kg/day. There was no evidence for carcinogenic potential associated with treprostinil inhalation in rats at systemic exposure levels up to about 34 and 1 times the human exposure, when based on Cmax and AUC of the average subcutaneous infusion rate achieved in clinical trials, respectively. In vitro and in vivo genetic toxicology studies did not demonstrate any mutagenic or clastogenic effects of treprostinil. Treprostinil sodium did not affect fertility or mating performance of male or female rats given continuous subcutaneous (sc) infusions at rates of up to 450 ng treprostinil/kg/min [about 59 times the recommended starting human sc infusion rate (1.25 ng/kg/min) and 8 times the average rate (9.3 ng/kg/min) achieved in clinical trials, on a ng/m^2 basis]. In this study, males were dosed from 10 weeks prior to mating and through the 2-week mating period. Females were dosed from 2 weeks prior to mating until gestational day 6.

Treprostinil diolamine did not demonstrate any carcinogenic effects in mouse or rat carcinogenicity studies. Oral administration of treprostinil diolamine to Tg.rasH2 mice at 0, 5, 10, and 20 mg/kg/day in males and 0, 3, 7.5, and 15 mg/kg/day in females daily for 26 weeks did not significantly increase the incidence of tumors. The exposures, when based on AUC, obtained at the highest dose levels used in males and females are about 7- and 15-fold, respectively, the human exposure of the average subcutaneous infusion rate achieved in clinical trials. Oral administration of treprostinil diolamine to Sprague Dawley rats at 0, 1, 3, and 10 mg/kg/day daily for 104 weeks did not significantly increase the incidence of tumors. The exposures obtained at the highest dose levels used in males and females are about 18- and 26-fold, respectively, the human exposure of the average subcutaneous infusion rate achieved in clinical trials.

Treprostinil diolamine was tested in vivo in a rat micronucleus assay and did not induce an increased incidence of micronucleated polychromatic erythrocytes.

14 CLINICAL STUDIES

14.1 Clinical Trials in Pulmonary Arterial Hypertension (PAH)

Two 12-week, multicenter, randomized, double-blind studies compared continuous subcutaneous infusion of Remodulin to placebo in a total of 470 patients with NYHA Class II (11%), III (81%), or IV (7%) PAH. PAH was idiopathic/heritable in 58% of patients, associated with connective tissue diseases in 19%, and the result of congenital systemic-to-pulmonary shunts in 23%. The mean age was 45 (range 9 to 75 years). About 81% were female and 84% were Caucasian. Pulmonary hypertension had been diagnosed for a mean of 3.8 years. The primary endpoint of the studies was change in 6-minute walking distance, a standard measure of exercise capacity. There were many assessments of symptoms related to heart failure, but local discomfort and pain associated with Remodulin may have substantially unblinded those assessments. The 6-minute walking distance and an associated subjective measurement of shortness of breath during the walk (Borg dyspnea score) were administered by a person not participating in other aspects of the study. Remodulin was administered as a subcutaneous infusion, described in Section 2, DOSAGE AND ADMINISTRATION, and the dose averaged 9.3 ng/kg/min at Week 12. Few subjects received doses greater than 40 ng/kg/min. Background therapy, determined by the investigators, could include anticoagulants, oral vasodilators, diuretics, digoxin, and oxygen, but not an endothelin receptor antagonist or epoprostenol. The two studies were identical in design and conducted simultaneously, and the results were analyzed both pooled and individually.

Hemodynamic Effects

As shown in Table 5, chronic therapy with Remodulin resulted in small hemodynamic changes consistent with pulmonary and systemic vasodilation.

Table 5: Hemodynamics during Chronic Administration of Remodulin in Patients with PAH in 12-Week Studies
Hemodynamic Parameter | Baseline |  | Mean change from baseline at Week 12
Hemodynamic Parameter | Remodulin (N=204-231) | Placebo (N=215-235) | Remodulin (N=163-199) | Placebo (N=182-215)
CI (L/min/m^2) | 2.4 ± 0.88 | 2.2 ± 0.74 | +0.12 ± 0.58 [Denotes statistically significant difference between Remodulin and placebo, p<0.05.] | -0.06 ± 0.55
PAPm (mmHg) | 62 ± 17.6 | 60 ± 14.8 | -2.3 ± 7.3 | +0.7 ± 8.5
RAPm (mmHg) | 10 ± 5.7 | 10 ± 5.9 | -0.5 ± 5.0 | +1.4 ± 4.8
PVRI (mmHg/L/min/m^2) | 26 ± 13 | 25 ± 13 | -3.5 ± 8.2 | +1.2 ± 7.9
SVRI (mmHg/L/min/m^2) | 38 ± 15 | 39 ± 15 | -3.5 ± 12 | -0.80 ± 12
SvO2 (%) | 62 ± 100 | 60 ± 11 | +2.0 ± 10 | -1.4 ± 8.8
SAPm (mmHg) | 90 ± 14 | 91 ± 14 | -1.7 ± 12 | -1.0 ± 13
HR (bpm) | 82 ± 13 | 82 ± 15 | -0.5 ± 11 | -0.8 ± 11
CI, cardiac index; PAPm, mean pulmonary arterial pressure; PVRI, pulmonary vascular resistance indexed; RAPm, mean right atrial pressure; SAPm, mean systemic arterial pressure; SVRI, systemic vascular resistance indexed; SvO2, mixed venous oxygen saturation; HR, heart rate

Clinical Effects

The effect of Remodulin on 6-minute walk, the primary endpoint of the 12-week studies, was small and did not achieve conventional levels of statistical significance. For the combined populations, the median change from baseline on Remodulin was 10 meters and the median change from baseline on placebo was 0 meters from a baseline of approximately 345 meters. Although it was not the primary endpoint of the study, the Borg dyspnea score was significantly improved by Remodulin during the 6-minute walk, and Remodulin also had a significant effect, compared with placebo, on an assessment that combined walking distance with the Borg dyspnea score. Remodulin also consistently improved indices of dyspnea, fatigue, and signs and symptoms of pulmonary hypertension, but these indices were difficult to interpret in the context of incomplete blinding to treatment assignment resulting from infusion site symptoms.

14.2 Flolan-To-Remodulin Transition Study

In an 8-week, multicenter, randomized, double-blind, placebo-controlled study, patients on stable doses of Flolan were randomly withdrawn from Flolan to placebo or Remodulin. Fourteen Remodulin and 8 placebo patients completed the study. The primary endpoint of the study was the time to clinical deterioration, defined as either an increase in Flolan dose, hospitalization due to PAH, or death. No patients died during the study.

During the study period, Remodulin effectively prevented clinical deterioration in patients transitioning from Flolan therapy compared to placebo (Figure 1). Thirteen of 14 patients in the Remodulin arm were able to transition from Flolan successfully, compared to only 1 of 8 patients in the placebo arm (p=0.0002).

Figure 1: Time to Clinical Deterioration for PAH Patients Transitioned from Flolan to Remodulin or Placebo in an 8-Week Study

16 HOW SUPPLIED/STORAGE AND HANDLING

Remodulin is supplied in 20-mL multidose vials as sterile solutions in water for injection, individually packaged in cartons. Unopened vials of Remodulin are stable until the date indicated when stored at 25°C (77°F), with excursions permitted to 2-30°C (36-86°F). A single vial of Remodulin should be used for no more than 30 days after the initial introduction into the vial.

Remodulin Injection is supplied as:

Remodulin | Concentration | NDC
2 mg / 20 mL | 0.1 mg/mL | 66302-111-01
4 mg / 20 mL | 0.2 mg/mL | 66302-112-01
8 mg / 20 mL | 0.4 mg/mL | 66302-114-01
20 mg / 20 mL | 1 mg/mL | 66302-101-01
50 mg / 20 mL | 2.5 mg/mL | 66302-102-01
100 mg / 20 mL | 5 mg/mL | 66302-105-01
200 mg / 20 mL | 10 mg/mL | 66302-110-01
400 mg / 20 mL | 20 mg/mL | 66302-120-01

STORAGE AND HANDLING

Sterile Diluent for Remodulin is supplied separately as:

50-mL vial, carton of 1 (NDC 66302-150-50).

17 PATIENT COUNSELING INFORMATION

Interruption of Therapy

Advise patients and caregivers to seek medical attention if they experience signs or symptoms of abrupt withdrawal of therapy or suspect a pump malfunction [see Warnings and Precautions (5.2)].

Overdose

Inform patients and their caregivers to seek medical attention if they experience signs or symptoms of Remodulin overdose [see Overdosage (10)].

©Copyright 2023 United Therapeutics Corp. All rights reserved.

REMODULIN manufactured for:

United Therapeutics Corp.
Research Triangle Park, NC 27709

PRINCIPAL DISPLAY PANEL - 0.1 mg/mL Vial Carton

REMODULIN®
(treprostinil) Injection

2 mg/20 mL
(0.1 mg/mL)

For Subcutaneous
and Intravenous Infusion

20 mL multidose vial

United
Therapeutics
CORPORATION

PRINCIPAL DISPLAY PANEL - 0.2 mg/mL Vial Carton

REMODULIN®
(treprostinil) Injection

4 mg/20 mL
(0.2 mg/mL)

For Subcutaneous
and Intravenous Infusion

20 mL multidose vial

United
Therapeutics
CORPORATION

PRINCIPAL DISPLAY PANEL - 0.4 mg/mL Vial Carton

REMODULIN®
(treprostinil) Injection

8 mg/20 mL
(0.4 mg/mL)

For Subcutaneous
and Intravenous Infusion

20 mL multidose vial

United
Therapeutics
CORPORATION

PRINCIPAL DISPLAY PANEL - 1 mg/mL Vial Carton

REMODULIN®
(treprostinil) Injection

20 mg/20 mL
(1 mg/mL)

For Subcutaneous
and Intravenous Infusion

20 mL multidose vial

United
Therapeutics
CORPORATION

PRINCIPAL DISPLAY PANEL - 2.5 mg/mL Vial Carton

REMODULIN®
(treprostinil) Injection

50 mg/20 mL
(2.5 mg/mL)

For Subcutaneous
and Intravenous Infusion

20 mL multidose vial

United
Therapeutics
CORPORATION

PRINCIPAL DISPLAY PANEL - 5 mg/mL Vial Carton

REMODULIN®
(treprostinil) Injection

100 mg/20 mL
(5 mg/mL)

For Subcutaneous
and Intravenous Infusion

20 mL multidose vial

United
Therapeutics
CORPORATION

PRINCIPAL DISPLAY PANEL - 10 mg/mL Vial Carton

REMODULIN®
(treprostinil) Injection

200 mg/20 mL
(10 mg/mL)

For Subcutaneous
and Intravenous Infusion

20 mL multidose vial

United
Therapeutics
CORPORATION

PRINCIPAL DISPLAY PANEL - 20 mg/mL Vial Carton

REMODULIN®
(treprostinil) Injection

400 mg/20 mL
(20 mg/mL)

For Subcutaneous
and Intravenous Infusion

20 mL multidose vial

United
Therapeutics
CORPORATION

PRINCIPAL DISPLAY PANEL - 50 mL Vial Carton

NDC 66302-150-50

STERILE DILUENT
FOR REMODULIN®

1 x 50 mL
VIAL

Contains drug diluent for use only
with Intravenous Infusion of
REMODULIN® (treprostinil) Injection

Each vial contains 94 mg glycine,
73.3 mg sodium chloride, sodium
hydroxide (added to adjust pH), and
Water for Injection.

For dilution information see package
insert for REMODULIN® (treprostinil)
Injection.

Store at 20 - 25°C (68 - 77°F), excursions
permitted to 15 - 30°C (59 - 86°F)
[See USP Controlled Room Temperature].

DO NOT FREEZE